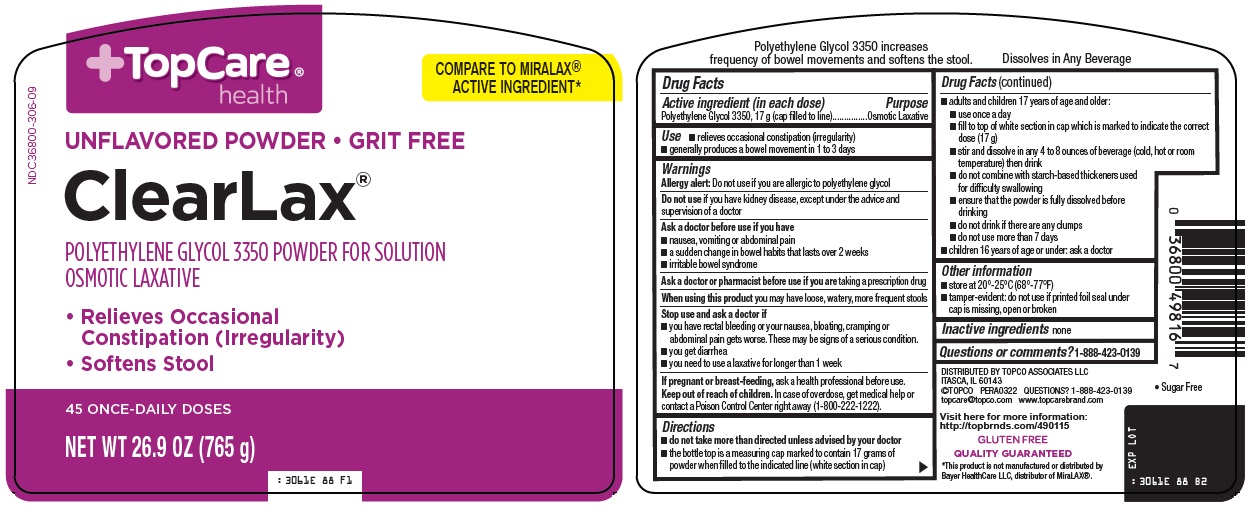 DRUG LABEL: Topcare ClearLax
NDC: 36800-306 | Form: POWDER, FOR SOLUTION
Manufacturer: Topco Associates LLC
Category: otc | Type: HUMAN OTC DRUG LABEL
Date: 20260219

ACTIVE INGREDIENTS: POLYETHYLENE GLYCOL 3350 17 g/17 g

Topco Associates LLC. ClearLax® Drug Facts

Active ingredient (in each dose)

Polyethylene Glycol 3350, 17 g (cap filled to line)

Purpose

Osmotic Laxative

Use

- relieves occasional constipation (irregularity)
- generally produces a bowel movement in 1 to 3 days

Warnings

Allergy alert: Do not use if you are allergic to polyethylene glycol

Do not use

if you have kidney disease, except under the advice and supervision of a doctor

Ask a doctor before use if you have

- nausea, vomiting or abdominal pain
- a sudden change in bowel habits that lasts over 2 weeks
- irritable bowel syndrome

Ask a doctor or pharmacist before use if you are

taking a prescription drug

When using this product

you may have loose, watery, more frequent stools

Stop use and ask a doctor if

- you have rectal bleeding or your nausea, bloating, cramping or abdominal pain gets worse. These may be signs of a serious condition.
- you get diarrhea
- you need to use a laxative for longer than 1 week

If pregnant or breast-feeding,

ask a health professional before use.

Keep out of reach of children.

In case of overdose, get medical help or contact a Poison Control Center right away (1-800-222-1222).

Directions

- do not take more than directed unless advised by your doctor
- the bottle top is a measuring cap marked to contain 17 grams of powder when filled to the indicated line (white section in cap)
- adults and children 17 years of age and older:
- use once a day
- fill to top of white section in cap which is marked to indicate the correct dose (17 g)
- stir and dissolve in any 4 to 8 ounces of beverage (cold, hot or room temperature) then drink
- do not combine with starch-based thickeners used for difficulty swallowing
- ensure that the powder is fully dissolved before drinking
- do not drink if there are any clumps
- use no more than 7 days
- children 16 years of age or under: ask a doctor

Other information

- store at 20˚-25˚C (68˚-77˚F)
- tamper-evident: do not use if printed foil seal under cap is missing, open or broken

Inactive ingredients

none

Questions or comments?

1-888-423-0139

Principal Display Panel

TopCare® health

COMPARE TO MIRALAX® ACTIVE INGREDIENT

UNFLAVORED POWDER • GRIT FREE

ClearLax®

POLYETHYLENE GLYCOL 3350 POWDER FOR SOLUTION

OSMOTIC LAXATIVE

• Relieves Occasional Constipation (Irregularity)

• Softens Stool

45 ONCE-DAILY DOSES

NET WT 26.9 OZ (765 g)